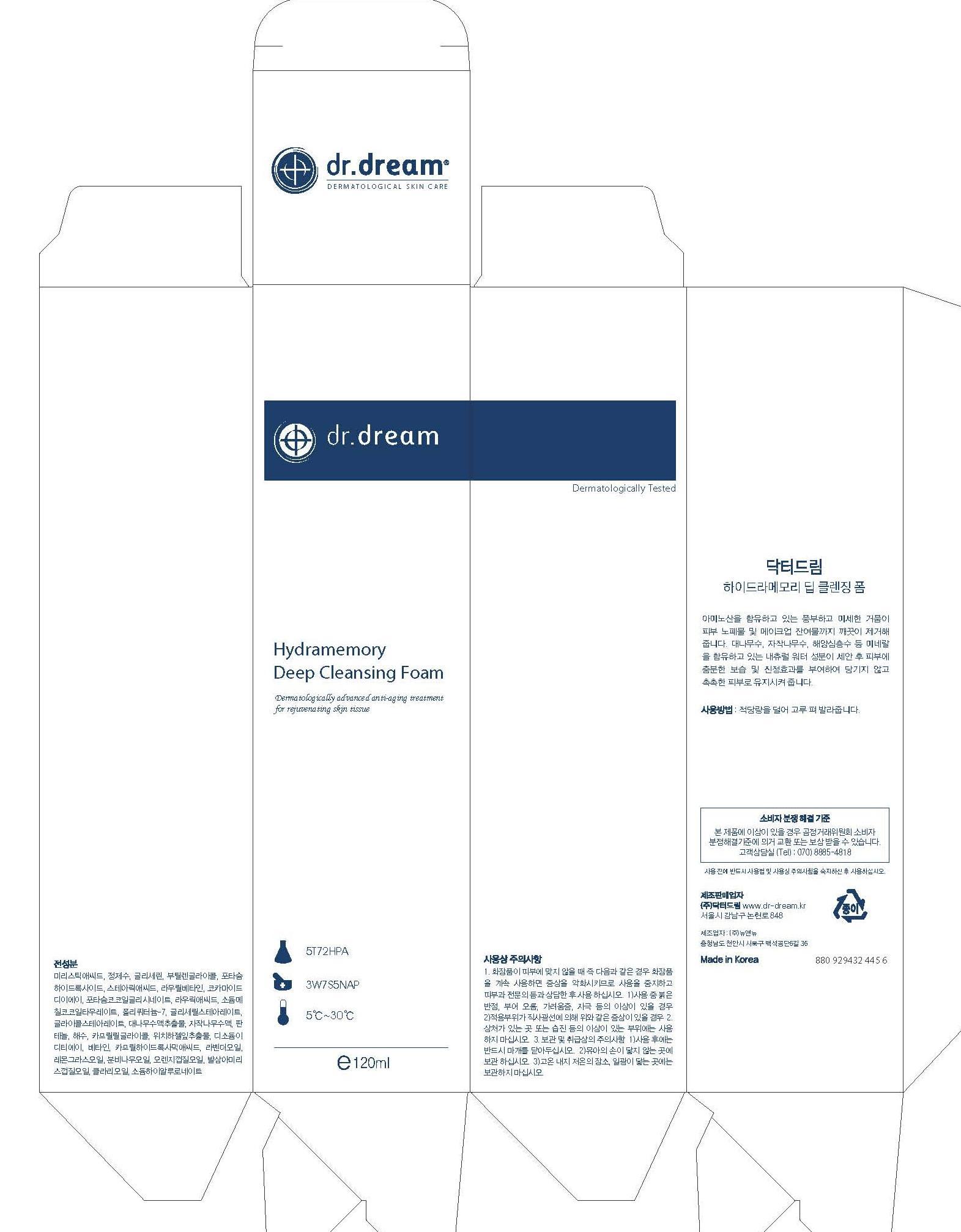 DRUG LABEL: Dr. Dream Hydramemory Deep Cleansing
NDC: 53077-9001 | Form: LIQUID
Manufacturer: Dr. Dream Inc
Category: otc | Type: HUMAN OTC DRUG LABEL
Date: 20120925

ACTIVE INGREDIENTS: WITCH HAZEL 0.1 mg/100 mL
INACTIVE INGREDIENTS: MUSA BASJOO WHOLE; ACETYL HEXAPEPTIDE-8; PALMITOYL OLIGOPEPTIDE; PALMITOYL TETRAPEPTIDE-7; POLYSORBATE 60; GLYCERIN; CAPRYLHYDROXAMIC ACID; ADENOSINE; AMMONIUM ACRYLOYLDIMETHYLTAURATE/VP COPOLYMER; NEOPENTYL GLYCOL; BLACK OLIVE; SODIUM CHONDROITIN SULFATE (PORCINE; 5500 MW); LAVANDULA ANGUSTIFOLIA FLOWERING TOP; CYMBOPOGON SCHOENANTHUS OIL; ABIES SIBIRICA LEAF OIL; ORANGE; AMYRIS BALSAMIFERA OIL; CLARY SAGE OIL; LECITHIN, SOYBEAN; SODIUM PHOSPHATE; HYALURONATE SODIUM; THIOREDOXIN; PREZATIDE COPPER; PALMITOYL PENTAPEPTIDE-4; GLYCINE; GLUTAMINE; LYSINE; LEUCINE; METHIONINE; VALINE; SERINE; CYSTEINE; CYSTINE; ASPARAGINE; ALANINE; ARGININE; ORNITHINE; ISOLEUCINE; TYROSINE; THREONINE; TRYPTOPHAN; PHENYLALANINE; PROLINE; HISTIDINE

Drug Facts

ACTIVE INGREDIENT

witch hazel

INACTIVE INGREDIENT

water, myristic acid, glycerin, butylene glycol, potassium hydroxide, stearic acid, lauryl betaine, lauric acid, cocamide dea, potassium cocoyl glycinate, sodium methyl cocoyl taurate, polyquaternium-7, glyceryl stearate, clycol stearate, bambusa vulgaris sap extract, betula alba juice, panthenol, sea water, orange peel oil, caprylyl glycol, disodium edta, betaine, caprylhydroxamic acid, bergamot fruit oil, pelargonium graveolens flower oil, cananga odorata flower oil, sodium hyaluronate

PURPOSE

general care

keep out of reach of the children

INDICATIONS AND USAGE

Carry out cleansing, as if you massage your entire face using foam, and then sufficiently rinse your face with warm water, after taking out the proper amount to your palm and making foams with soft and warm water. It would be much better to apply patting with cold water to your face while you are rinsing your face in the end.

When using this product
- keep out of eyes, ears, and mouth. If contact occurs, rinse with plenty of cold water right away and contact a physician. If swallowing, drink plenty of water and contact a physician

DOSAGE AND ADMINISTRATION

for external use only